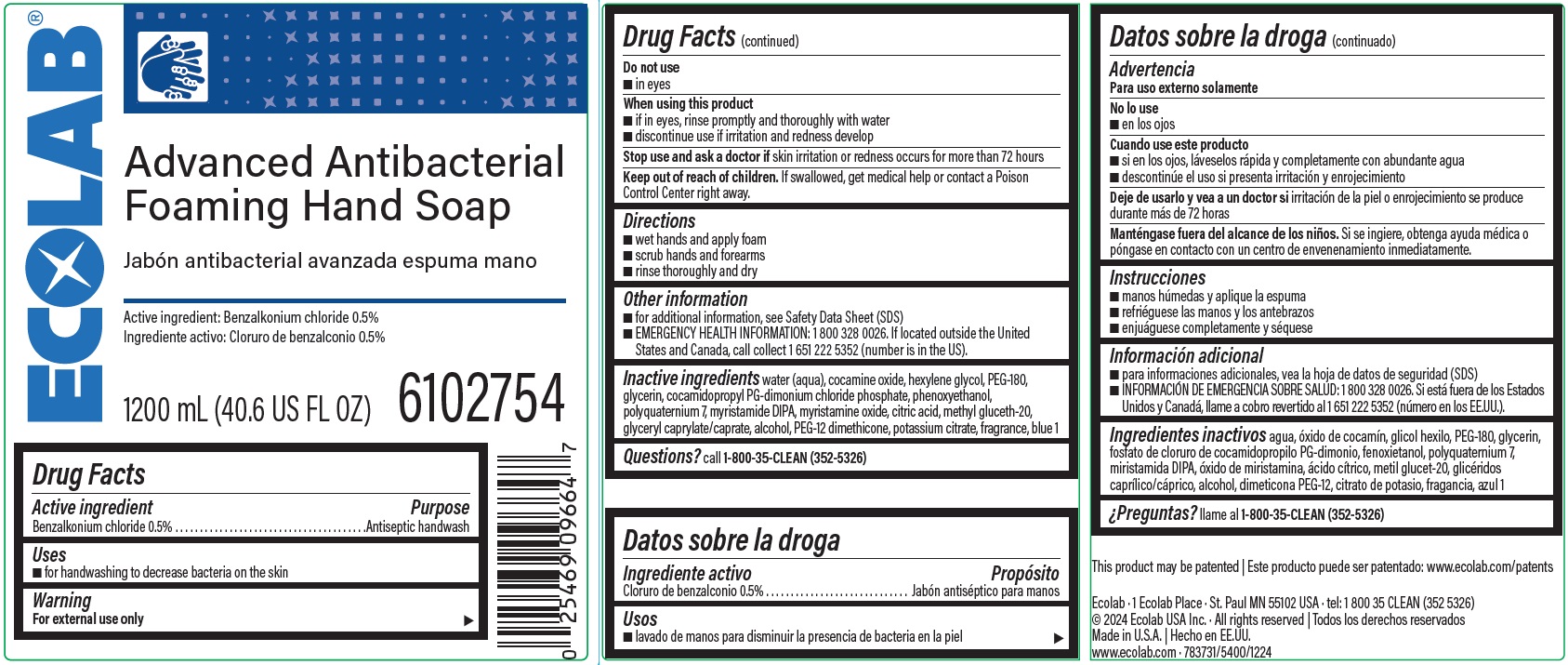 DRUG LABEL: Advanced Antibacterial Foaming Hand Soap
NDC: 47593-543 | Form: SOLUTION
Manufacturer: Ecolab Inc.
Category: otc | Type: HUMAN OTC DRUG LABEL
Date: 20251231

ACTIVE INGREDIENTS: BENZALKONIUM CHLORIDE 5 mg/1 mL
INACTIVE INGREDIENTS: WATER; COCAMINE OXIDE; HEXYLENE GLYCOL; POLYETHYLENE GLYCOL 8000; GLYCERIN; COCAMIDOPROPYL PG-DIMONIUM CHLORIDE PHOSPHATE; PHENOXYETHANOL; POLYQUATERNIUM-7 (70/30 ACRYLAMIDE/DADMAC; 1600000 MW); MYRISTIC DIISOPROPANOLAMIDE; MYRISTAMINE OXIDE; CITRIC ACID MONOHYDRATE; METHYL GLUCETH-20; GLYCERYL MONO- AND DICAPRYLOCAPRATE; ALCOHOL; PEG-12 DIMETHICONE; POTASSIUM CITRATE; FD&C BLUE NO. 1

Drug Facts

Active Ingredient

Benzalkonium chloride 0.5%

Purpose

Antiseptic handwash

Uses

- for handwashing to decrease bacteria on the skin

Warning

- For external use only

Do not use

- in eyes

When using the product

- if in eyes, rinse promptly and thoroughly with water
- discontinue use if irritation and redness develop

Stop use and ask a doctor if skin irritation or redness occurs for more than 72 hours

Keep out of reach of children. If swallowed, get medical help or contact a Poison Control Center right away.

Directions

- wet hands and apply foam
- scrub hands and forearms
- rinse thoroughly and dry

Other information

- for additional information, see Safety Data Sheet (SDS)
- EMERGENCY HEALTH INFORMATION: 1 800 328 0026. If located outside the United States and Canada, call collect 1 651 222 5352 (number is in the US

INACTIVE INGREDIENT

Inactive ingredients water (aqua), cocamine oxide, hexylene glycol, PEG-180, glycerin, cocamidopropyl PG-dimonium chloride phosphate, phenoxyethanol, polyquaternium 7, myristamide DIPA, myristamine oxide, citric acid, methyl gluceth-20, glyceryl caprylate/caprate, alcohol, PEG-12 dimethicone, potassium citrate, fragrance, blue 1

Questions? call 1-800-35-CLEAN (352-5326)

Representative Label and Principal Display Panel

Ecolab®

Advanced Antibacterial

Foaming Hand Soap

Active ingredient: Benzalkonium chloride 0.5%

1200 mL (40.6 US FL OZ) 6102754

Ecolab · 1 Ecolab Place · St. Paul MN 55102 USA ·

tel: 1 800 35 CLEAN (352 5326)

© 2024 Ecolab USA Inc. · All rights reserved

Made in U.S.A.

www.ecolab.com